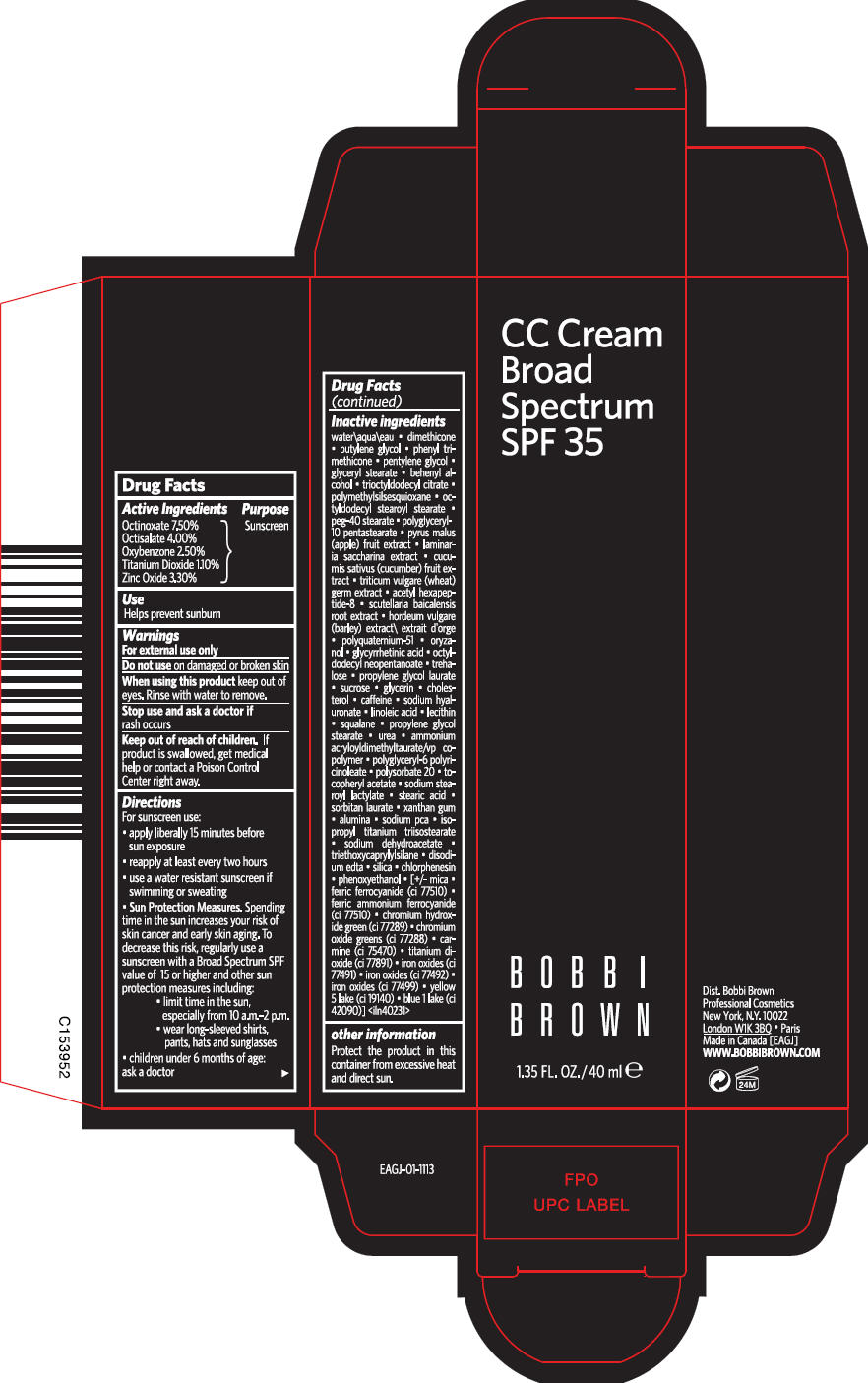 DRUG LABEL: Bobbi Brown CC BROAD SPECTRUM SPF 25
NDC: 64141-018 | Form: CREAM
Manufacturer: Bobbi Brown Professional Cosmetics Inc.
Category: otc | Type: HUMAN OTC DRUG LABEL
Date: 20210812

ACTIVE INGREDIENTS: OCTINOXATE 0.08175 g/100 mL; OCTISALATE 0.0436 g/100 mL; OXYBENZONE 0.02725 g/100 mL; TITANIUM DIOXIDE 0.01199 g/100 mL; ZINC OXIDE 0.03597 g/100 mL
INACTIVE INGREDIENTS: WATER; DIMETHICONE; BUTYLENE GLYCOL; PHENYL TRIMETHICONE; PENTYLENE GLYCOL; GLYCERYL MONOSTEARATE; DOCOSANOL; TRIOCTYLDODECYL CITRATE; OCTYLDODECYL STEAROYL STEARATE; PEG-40 STEARATE; APPLE; SACCHARINA LATISSIMA; CUCUMBER; WHEAT GERM; ACETYL HEXAPEPTIDE-8; SCUTELLARIA BAICALENSIS ROOT; ORYZANOL; ENOXOLONE; OCTYLDODECYL NEOPENTANOATE; TREHALOSE; PROPYLENE GLYCOL MONOLAURATE; SUCROSE; GLYCERIN; CHOLESTEROL; CAFFEINE; HYALURONATE SODIUM; LINOLEIC ACID; SQUALANE; PROPYLENE GLYCOL MONOSTEARATE; UREA; AMMONIUM ACRYLOYLDIMETHYLTAURATE/VP COPOLYMER; POLYSORBATE 20; .ALPHA.-TOCOPHEROL ACETATE; SODIUM STEAROYL LACTYLATE; STEARIC ACID; SORBITAN MONOLAURATE; XANTHAN GUM; ALUMINUM OXIDE; SODIUM PYRROLIDONE CARBOXYLATE; ISOPROPYL TITANIUM TRIISOSTEARATE; SODIUM DEHYDROACETATE; TRIETHOXYCAPRYLYLSILANE; EDETATE DISODIUM; SILICON DIOXIDE; CHLORPHENESIN; PHENOXYETHANOL; MICA; FERRIC FERROCYANIDE; FERRIC AMMONIUM FERROCYANIDE; CHROMIC OXIDE; CARMINIC ACID; FERRIC OXIDE RED; FERRIC OXIDE YELLOW; FERROSOFERRIC OXIDE; FD&C YELLOW NO. 5; FD&C BLUE NO. 1

Bobbi Brown CC CREAM BROAD SPECTRUM SPF 25

Drug Facts

Active Ingredients

Octinoxate 7.50%
Octisalate 4.00%
Oxybenzone 2.50%
Titanium Dioxide 1.10%
Zinc Oxide 3.30%

Purpose

Sunscreen

Use

Helps prevent sunburn

Warnings

For external use only

Do not use on damaged or broken skin

When using this product keep out of eyes. Rinse with water to remove.

Stop use and ask a doctor if rash occurs

Keep out of reach of children. If product is swallowed, get medical help or contact a Poison Control Center right away.

Directions

For sunscreen use:

- apply liberally 15 minutes before sun exposure
- reapply at least every two hours
- use a water resistant sunscreen if swimming or sweating
- Sun Protection Measures. Spending time in the sun increases your risk of skin cancer and early skin aging. To decrease this risk, regularly use a sunscreen with a Broad Spectrum SPF value of 15 or higher and other sun protection measures including:
  - limit time in the sun, especially from 10 a.m.-2 p.m.
  - wear long-sleeved shirts, pants, hats and sunglasses
- children under 6 months of age: ask a doctor

Inactive ingredients

water\aqua\eau • dimethicone • butylene glycol • phenyl trimethicone • pentylene glycol • glyceryl stearate • behenyl alcohol • trioctyldodecyl citrate • polymethylsilsesquioxane • octyldodecyl stearoyl stearate • peg-40 stearate • polyglyceryl-10 pentastearate • pyrus malus (apple) fruit extract • laminaria saccharina extract • cucumis sativus (cucumber) fruit extract • triticum vulgare (wheat) germ extract • acetyl hexapeptide-8 • scutellaria baicalensis root extract • hordeum vulgare (barley) extract\ extrait d'orge • polyquaternium-51 • oryzanol • glycyrrhetinic acid • octyldodecyl neopentanoate • trehalose • propylene glycol laurate • sucrose • glycerin • cholesterol • caffeine • sodium hyaluronate • linoleic acid • lecithin • squalane • propylene glycol stearate • urea • ammonium acryloyldimethyltaurate/vp copolymer • polyglyceryl-6 polyricinoleate • polysorbate 20 • tocopheryl acetate • sodium stearoyl lactylate • stearic acid • sorbitan laurate • xanthan gum • alumina • sodium pca • isopropyl titanium triisostearate • sodium dehydroacetate • triethoxycaprylylsilane • disodium edta • silica • chlorphenesin • phenoxyethanol • [+/- mica • ferric ferrocyanide (ci 77510) • ferric ammonium ferrocyanide (ci 77510) • chromium hydroxide green (ci 77289) • chromium oxide greens (ci 77288) • carmine (ci 75470) • titanium dioxide (ci 77891) • iron oxides (ci 77491) • iron oxides (ci 77492) • iron oxides (ci 77499) • yellow 5 lake (ci 19140) • blue 1 lake (ci 42090)] <iln40231>

other information

Protect the product in this container from excessive heat and direct sun.

PRINCIPAL DISPLAY PANEL - 40 ml Tube Carton

CC Cream
Broad
Spectrum
SPF 35

BOBBI
BROWN

1.35 FL. OZ./40 ml e